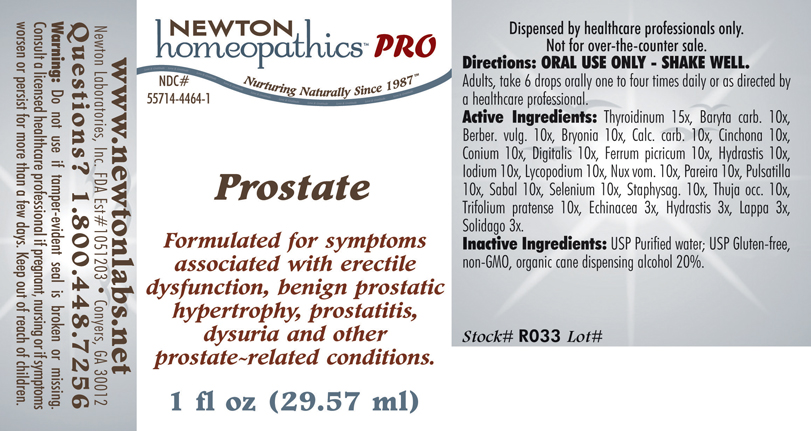 DRUG LABEL: Prostate 
NDC: 55714-4464 | Form: LIQUID
Manufacturer: Newton Laboratories, Inc.
Category: homeopathic | Type: HUMAN PRESCRIPTION DRUG LABEL
Date: 20110601

ACTIVE INGREDIENTS: Thyroid, Unspecified 15 [hp_X]/1 mL; Barium Carbonate 10 [hp_X]/1 mL; Berberis Vulgaris Root Bark 10 [hp_X]/1 mL; Bryonia Alba Root 10 [hp_X]/1 mL; Oyster Shell Calcium Carbonate, Crude 10 [hp_X]/1 mL; Cinchona Officinalis Bark 10 [hp_X]/1 mL; Conium Maculatum Flowering Top 10 [hp_X]/1 mL; Digitalis 10 [hp_X]/1 mL; Ferric Picrate 10 [hp_X]/1 mL; Goldenseal 10 [hp_X]/1 mL; Iodine 10 [hp_X]/1 mL; Lycopodium Clavatum Spore 10 [hp_X]/1 mL; Strychnos Nux-vomica Seed 10 [hp_X]/1 mL; Chondrodendron Tomentosum Root 10 [hp_X]/1 mL; Pulsatilla Vulgaris 10 [hp_X]/1 mL; Saw Palmetto 10 [hp_X]/1 mL; Selenium 10 [hp_X]/1 mL; Delphinium Staphisagria Seed 10 [hp_X]/1 mL; Thuja Occidentalis Leafy Twig 10 [hp_X]/1 mL; Trifolium Pratense Flower 10 [hp_X]/1 mL; Echinacea, Unspecified 3 [hp_X]/1 mL; Goldenseal 3 [hp_X]/1 mL; Arctium Lappa Root 3 [hp_X]/1 mL; Solidago Virgaurea Flowering Top 3 [hp_X]/1 mL
INACTIVE INGREDIENTS: Alcohol

Prostate

PRODUCT NAME & INDICATIONS SECTION

Prostate Formulated for symptoms associated with erectile dysfunction, benign prostatic hypertrophy, prostatitis, dysuria and other prostate related conditions.

DIRECTION SECTION

Directions: ORAL USE ONLY - SHAKE WELL. Adults, take 6 drops orally one to four times daily or as directed by a healthcare professional.

ACTIVE INGREDIENT SECTION

Thyroidinum 15x, Baryta carb. 10x ,Berber. vulg. 10x, Bryonia 10x, Calc. carb. 10x, Cinchona 10x ,Conium 10x, Digitalis 10x, Ferrum picricum 10x, Hydrastis 10x, Iodium 10x, Lycopodium 10x, Nux vom. 10x, Pareira 10x, Pulsatilla 10x, Sabal 10x, Selenium 10x, Staphysag. 10x, Thuja occ. 10x, Trifolium pratense 10x, Echinacea 3x, Hydrastis 3x, Lappa 3x, Solidago 3x.

PURPOSE SECTION

Formulated for symptoms associated with erectile dysfunction, benign prostatic hypertrophy, prostatitis, dysuria and other prostate related conditions.

INACTIVE INGREDIENT SECTION

USP Purified water; USP Gluten-free,non-GMO, organic cane dispensing alcohol 20%.

QUESTIONS? SECTION

www.newtonlabs.net Newton Laboratories, Inc. FDA Est # 1051203 - Conyers, GA30012
Questions? 1.800.448.7256

WARNINGS SECTION

Warning: Do not use if tamper - evident seal is broken or missing. Consult a licensed healthcare professional if pregnant, nursing or if symptoms worsen or persist for more than a few days. Keep out of reach of children.

OTC - PREGNANCY OR BREAST FEEDING SECTION

Consult a licensed healthcare professional if pregnant, nursing or if symptoms worsen or persist for more than a few days.

OTC - KEEP OUT OF REACH OF CHILDREN SECTION

Keep out of reach of children